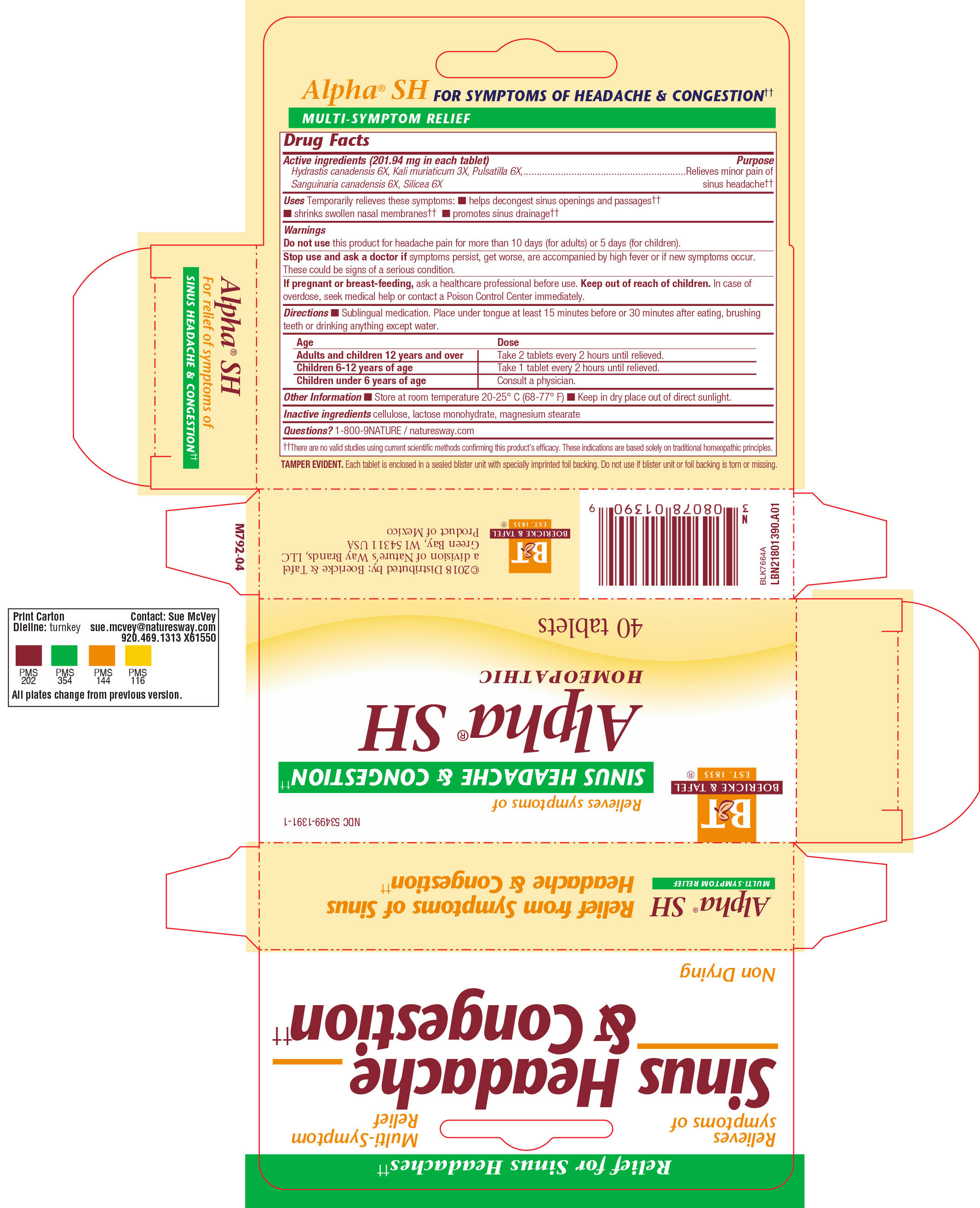 DRUG LABEL: ALPHA SH
NDC: 53499-1391 | Form: TABLET
Manufacturer: Schwabe North America, Inc.
Category: homeopathic | Type: HUMAN OTC DRUG LABEL
Date: 20220322

ACTIVE INGREDIENTS: SANGUINARIA CANADENSIS ROOT 6 [hp_X]/1 1; GOLDENSEAL 6 [hp_X]/1 1; SILICON DIOXIDE 6 [hp_X]/1 1; POTASSIUM CHLORIDE 3 [hp_X]/1 1; PULSATILLA VULGARIS 6 [hp_X]/1 1
INACTIVE INGREDIENTS: LACTOSE MONOHYDRATE; MAGNESIUM STEARATE; CELLULOSE, MICROCRYSTALLINE

Alpha SH

Active Ingedients

Hydrastis canadensis 6X

Kali muriaticum 3X

Pulsatilla 6X

Sanguinaria canadensis 6X

Silicea 6X

Inactive Ingredient

Cellulose

Lactose monohydrate

Magnesium stearate

Purpose

Temporarily relieves these symptoms: helps decongest sinus openings and passages, shrinks swollen nasal membranes and promotes sinus drainage.

Indications and Usage

Temporarily relieves these symptoms: helps decongest sinus openings and sinus passages, shrinks swollen nasal membranse, promotes sinus drainage.

Dosage & Administration

Directions: Sublingual medication. Place under tongue at least 15 minutes before or 30 minutes after eating, brushing teeth or drinking anything except water.

Adults and Children 12 years and over: Take 2 tablets every 2 hours until relieved

Children 6-12 years of age: take 1 tablet every 2 hours until relieved

Children under 6 years of age: Consult a physician.

Warnings

Do not use this product for headache pain for more than 10 days (for adults) or 5 days (for children).

Stop Use

Stop use and ask a doctor if symptoms persist, get worse, or are accompanied by a high fever, or if new symptoms occur.
These can be signs of a serious condition.

Pregnancy or Breast Feeding

If you are pregnant or breast-feeding, ask a healthcare professional before use.

Keep out of reach of children

Overdose

In case of overdose, seek medical help or contact a Poison Control immediately.